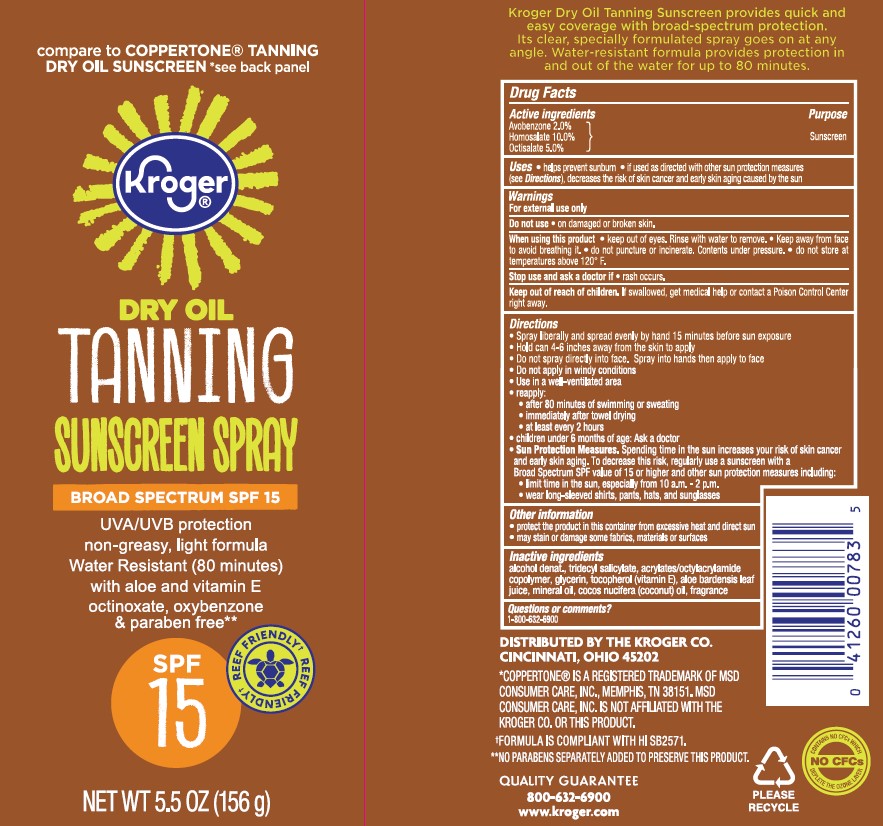 DRUG LABEL: Kroger Dry Oil Tanning Sunscreen Broad Spectrum SPF 15 Reef Friendly
NDC: 30142-934 | Form: SPRAY
Manufacturer: THE KROGER COMPANY
Category: otc | Type: HUMAN OTC DRUG LABEL
Date: 20241015

ACTIVE INGREDIENTS: AVOBENZONE 20 mg/1 g; HOMOSALATE 100 mg/1 g; OCTISALATE 50 mg/1 g
INACTIVE INGREDIENTS: ALCOHOL; ACRYLATE/ISOBUTYL METHACRYLATE/N-TERT-OCTYLACRYLAMIDE COPOLYMER (75000 MW); GLYCERIN; ALOE VERA LEAF; .ALPHA.-TOCOPHEROL, DL-; COCONUT OIL; MINERAL OIL; TRIDECYL SALICYLATE

Kroger Dry Oil Tanning Sunscreen Spray Broad Spectrum SPF 15 Reef Friendly

Active ingredients

Avobenzone 2.0%, Homosalate 10.0%, Octisalate 5.0%

Purpose

Sunscreen

Uses

- helps prevent sunburn
- if used as directed with other sun protection measures (see Directions), decreases the risk of skin cancer and early skin aging caused by the sun

Warnings

For external use only

FLAMMABLE:

• do not use near heat, flame or while smoking
• avoid long term storage above 104°F (40°C)

Do not use

- on damaged or broken skin

When using this product • keep out of eyes. Rinse with water to remove. • do not puncture or incinerate. Contents under pressure. • do not store at temperatures above 120° F.

Stop use and ask doctor if

- rash occurs.

Keep out of reach of children. If product is swallowed, get medical help or contact a Poison Control Center right away.

Directions

•spray liberally and spread evenly by hand15 minutes before sun exposure
• hold can 4-6 inches away from the skin to apply
• do not spray into face. Spray into hands, then apply to face.

• do not apply in windy conditions

• use in well-ventilated areas
reapply:
• after 80 minutes of swimming or sweating
• immediately after towel drying
• at least every 2 hours

• children under 6 months: Ask a doctor
Sun Protection Measures. Spending time in the sun increases your risk of skin cancer and early skin aging. To decrease this risk, regularly use a sunscreen with a Broad Spectrum SPF value of 15 or higher and other sun protection measures including:
• limit time in the sun, especially from 10 a.m. - 2 p.m.
• wear long-sleeved shirts, pants, hats, and sunglasses

Other Information

• protect the product in this container from excessive heat and direct sun
• may stain or damage some fabrics, materials, or surfaces

Inactive ingredients

alcohol denat., tridecyl salicylate, acrylates/octylacrylamide copolymer, glycerin, tocopherol (vitamin E), aloe barbadensis leaf extract, mineral oil, cocos nucifera (coconut) oil, fragrance.